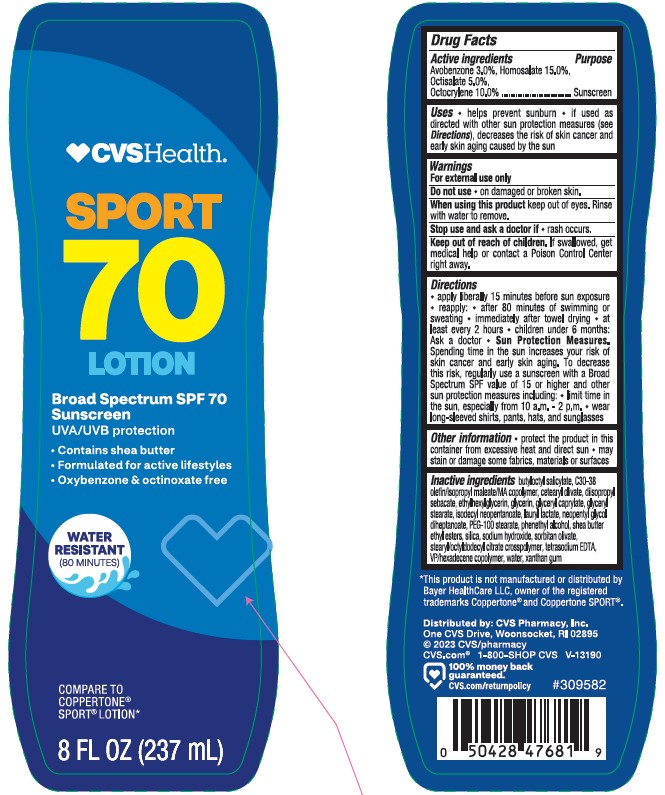 DRUG LABEL: CVS Health Sport 70
NDC: 51316-056 | Form: LOTION
Manufacturer: CVS PHARMACY
Category: otc | Type: HUMAN OTC DRUG LABEL
Date: 20241017

ACTIVE INGREDIENTS: OCTISALATE 50 mg/1 mL; HOMOSALATE 150 mg/1 mL; AVOBENZONE 30 mg/1 mL; OCTOCRYLENE 100 mg/1 mL
INACTIVE INGREDIENTS: SHEA BUTTER ETHYL ESTERS; DIISOPROPYL SEBACATE; PHENYLETHYL ALCOHOL; BUTYLOCTYL SALICYLATE; GLYCERYL CAPRYLATE; ISODECYL NEOPENTANOATE; ETHYLHEXYLGLYCERIN; PEG-100 STEARATE; GLYCERYL 1-STEARATE; CETEARYL OLIVATE; SORBITAN OLIVATE; VINYLPYRROLIDONE/HEXADECENE COPOLYMER; XANTHAN GUM; WATER; GLYCERIN; SODIUM HYDROXIDE; STEARYL/OCTYLDODECYL CITRATE CROSSPOLYMER; EDETATE SODIUM; NEOPENTYL GLYCOL DIHEPTANOATE; LAURYL LACTATE; SILICON DIOXIDE

CVS Health Sport 70 Lotion

Active ingredients

Avobenzone 3.0%,

Homosalate 15.0%,

Octisalate 5.0%

Octocrylene 10.0%

Purpose

Sunscreen

Uses

- helps prevent sunburn
- if used as directed with other sun protection measures (see Directions), decreases the risk of skin cancer and early skin aging caused by the sun

Warnings

For external use only

Do not use

• on damaged or broken skin.

When using this product

• keep out of eyes. Rinse with water to remove.

Stop use and ask a doctor if

• rash occurs.

Keep out of reach of children.

If swallowed, get medical help or contact a Poison Control Center right away.

Directions

- apply liberally 15 minutes before sun exposure
- use a water resistant sunscreen if swimming or sweating
- reapply at least every 2 hours
- children under 6 months of age: Ask a doctor
- Sun Protection Measures. Spending time in the sun increases your risk of skin cancer and early skin aging. To decrease this risk, regularly use a sunscreen with a Broad Spectrum SPF value of 15 or higher and other sun protection measures including:

• limit time in the sun, especially from 10 a.m. - 2 p.m.

• wear long-sleeved shirts, pants, hats, and sunglasses

Other information

- protect the product in this container from excessive heat and direct sun
- may stain or damage some fabrics, materials or surfaces

Inactive ingredients

butyloctyl salicylate, C30-38 olefin/isopropyl maleate/MA copolymer cetearyl olivate, diisopropyl sebacate, ethylhexylglycerin, glycerin, glyceryl caprylate, glyceryl stearate, isodecyl neopentanoate, lauryl lactate, neopentyl glycol diheptanoate, PEG-100 stearate, phenethyl alcohol, shea butter ethyl esters, silica, sodium hydroxide, sorbitan olivate, stearyl/octyldodecyl citrate crosspolymer, tetrasodium edta, VP/hexadecene copolymer, water , xanthan gum